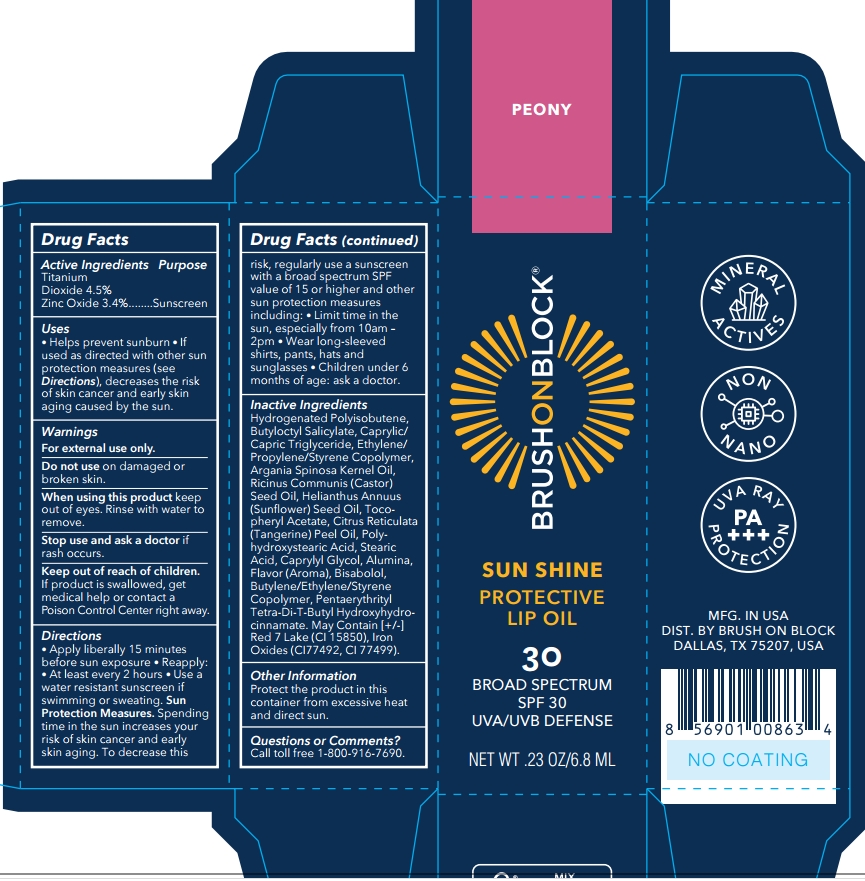 DRUG LABEL: Brush On Block Sun Shine SPF 30 Protective Lip Oil Peony Tint
NDC: 58274-024 | Form: OIL
Manufacturer: SPF Ventures LLC
Category: otc | Type: HUMAN OTC DRUG LABEL
Date: 20250203

ACTIVE INGREDIENTS: ZINC OXIDE 3.4 g/100 mL; TITANIUM DIOXIDE 4.5 g/100 mL
INACTIVE INGREDIENTS: ALUMINA; BUTYLATED HYDROXYTOLUENE; ARGANIA SPINOSA KERNEL OIL; HELIANTHUS ANNUUS (SUNFLOWER) SEED OIL; HYDROGENATED POLYISOBUTENE (450 MW); BISABOLOL; ETHYLHEXYL PALMITATE; CITRUS NOBILIS (MANDARIN ORANGE) PEEL OIL; CI 15850; PENTAERYTHRITYL TETRA-DI-T-BUTYL HYDROXYHYDROCINNAMATE; POLYHYDROXYSTEARIC ACID (2300 MW); BUTYLOCTYL SALICYLATE; CAPRYLYL GLYCOL; IRON OXIDES; STEARIC ACID; .ALPHA.-TOCOPHEROL ACETATE; CAPRYLIC/CAPRIC TRIGLYCERIDE; RICINUS COMMUNIS (CASTOR) SEED OIL

Brush On Block Sun Shine SPF 30 Protective Lip Oil Peony Tint

Active ingredients

titanium dioxide 4.5%

zinc oxide 3.4%

Purpose

Sunscreen

Uses

- Helps prevent sunburn
- If used as directed with other sun protection measures (see Directions), decreases the risk of skin cance and early skin aging caused by the sun.

Warnings

For external use only

When using this product keep out of eyes. Rinse with water to remove.

Do not use on damaged or broken skin.

Stop use and ask a doctor if rash occurs.

Keep out of reach of children，If product is swallowed, get medical help or contact a Poison Control Center right away.

Directions

- Apply liberally 15 minutes before sun exposure
- Reapply: After 80 minutes of swimming or sweating; Immediately after towel drying; At least every 2 hours.

Sun Protection Measures. Spending time in the sun increases your risk of skin cance and early skin aging. To decrease this risk, regularly use a sunscreen with a broad spectrum SPF value of 15 or higher and other sun protection measures including:Limit time in the sun especially from 10am-2pm; Wear long-sleeved shirts, pants, hats and subglasses; Children under 6 months: ask a doctor.

Inactive ingredients

ALUMINA

ARGANIA SPINOSA KERNEL OIL

BISABOLOL

BUTYLENE/ETHYLENE/STYRENE COPOLYMER

BUTYLOCTYL SALICYLATE

CAPRYLIC/CAPRIC TRIGLYCERIDE

CAPRYLYL GLYCOL

CITRUS RETICULATA (TANGERINE) PEEL OIL

ETHYLENE/PROPYLENE/STYRENE COPOLYMER

FLAVOR

HELIANTHUS ANNUUS (SUNFLOWER) SEED OIL

HYDROGENATED POLYISOBUTENE

IRON OXIDES

PENTAERYTHRITYL TETRA-DI-T-BUTYL HYDROXYHYDROCINNAMATE

POLYHYDROXYSTEARIC ACID

RICINUS COMMUNIS (CASTOR) SEED OIL

STEARIC ACID

TOCOPHERYL ACETATE

Other Information

Protect the production in this container from excessive heat and direct sun.